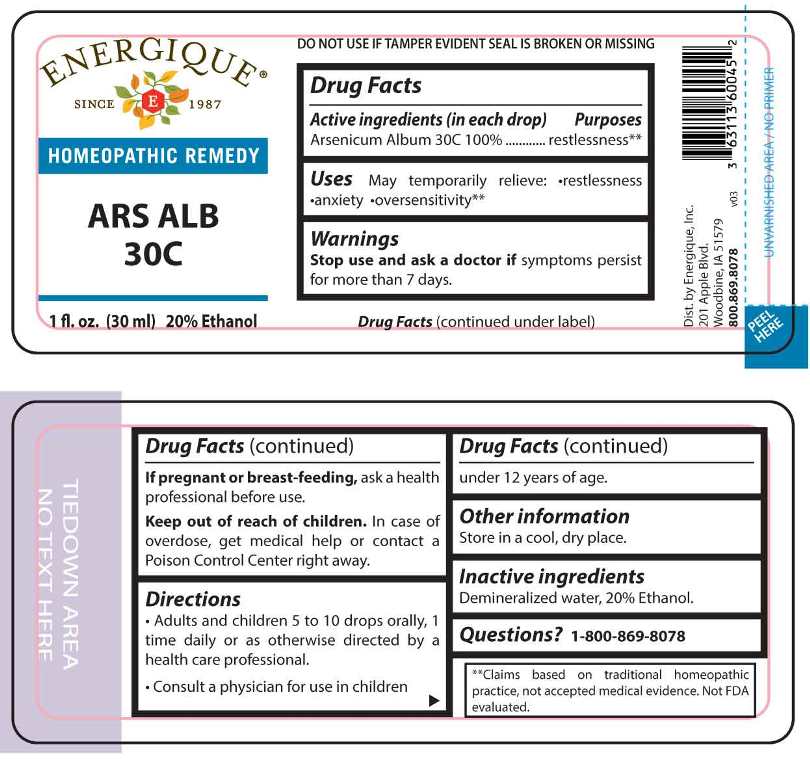 DRUG LABEL: Ars Alb
NDC: 44911-0146 | Form: LIQUID
Manufacturer: Energique, Inc.
Category: homeopathic | Type: HUMAN OTC DRUG LABEL
Date: 20250425

ACTIVE INGREDIENTS: ARSENIC TRIOXIDE 30 [hp_C]/1 mL
INACTIVE INGREDIENTS: WATER; ALCOHOL

DRUG FACTS:

ACTIVE INGREDIENT:

(in each drop) Arsenicum Album 30C 100%.

PURPOSES:

Arsenicum Album - restlessness**

**Claims based on traditional homeopathic practices, not accepted medical evidence. Not FDA evaluated.

USES:

May temporarily relieve:

•restlessness •anxiety oversensitivity.**

**Claims based on traditional homeopathic practice, not accepted medical evidence. Not FDA evaluated.

WARNINGS:

Stop use and ask a doctor if symptoms persist for more than 7 days.

If pregnant or breast-feeding, ask a health professional before use.

Keep out of reach of children. In case of overdose, get medical help or contact a Poison Control Center right away.

DO NOT USE IF TAMPER EVIDENT SEAL IS BROKEN OR MISSING

Store in a cool, dry place.

Keep out of reach of children. In case of overdose, get medical help or contact a Poison Control Center right away.

DIRECTIONS:

• Adults and children 5 to 10 drops orally, 1 time daily or as otherwise directed by a health care professional.

• Consult a physician for use in children under 12 years of age.

INACTIVE INGREDIENTS:

Demineralized water, 20% Ethanol.

QUESTIONS:

Dist. by Energique, Inc.

201 Apple Blvd

Woodbine, IA 51579

800-869-8078

PACKAGE LABEL DISPLAY:

ENERGIQUE
SINCE 1987
HOMEOPATHIC REMEDY
ARS ALB

30C
1 fl. oz. (30 ml)